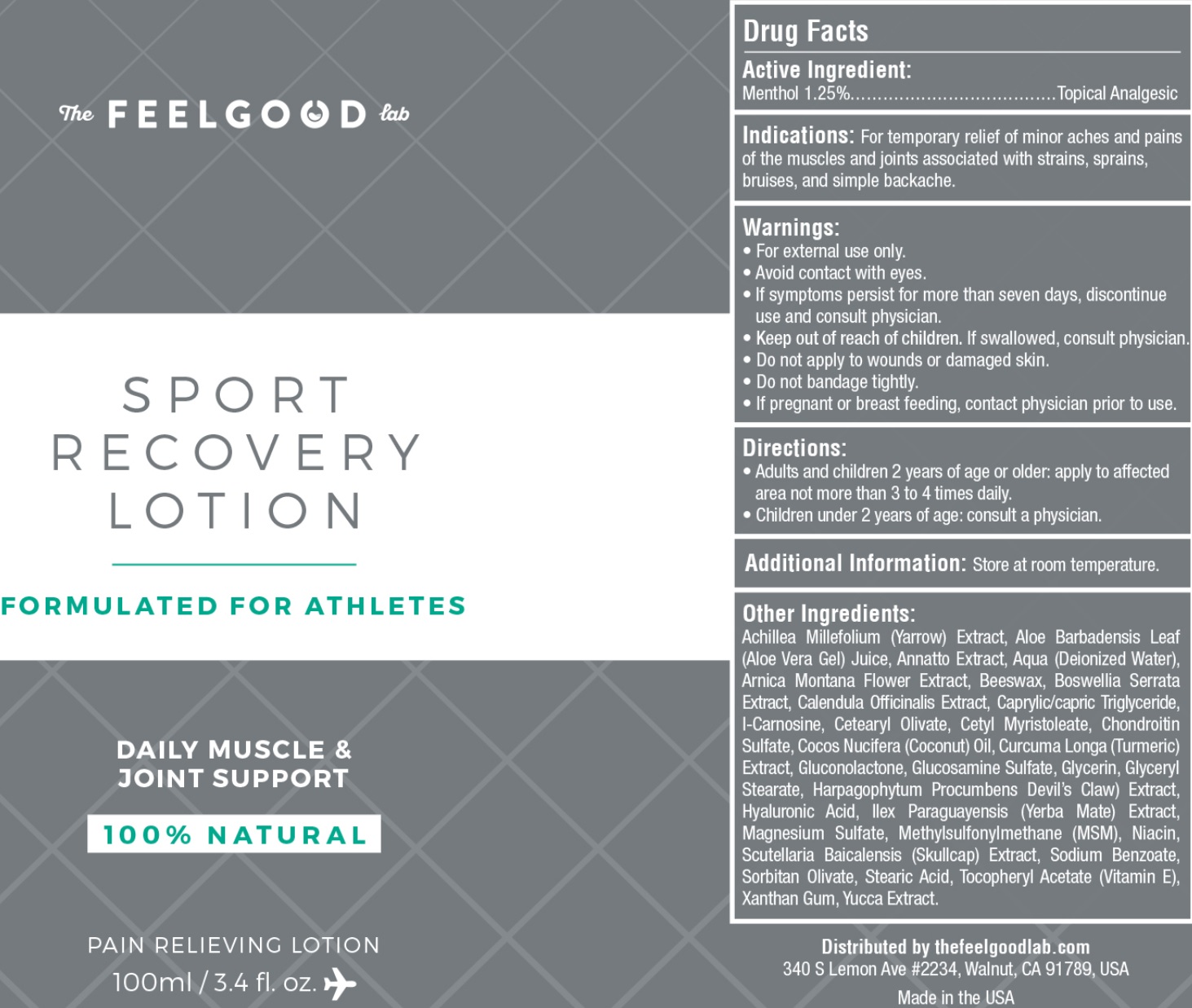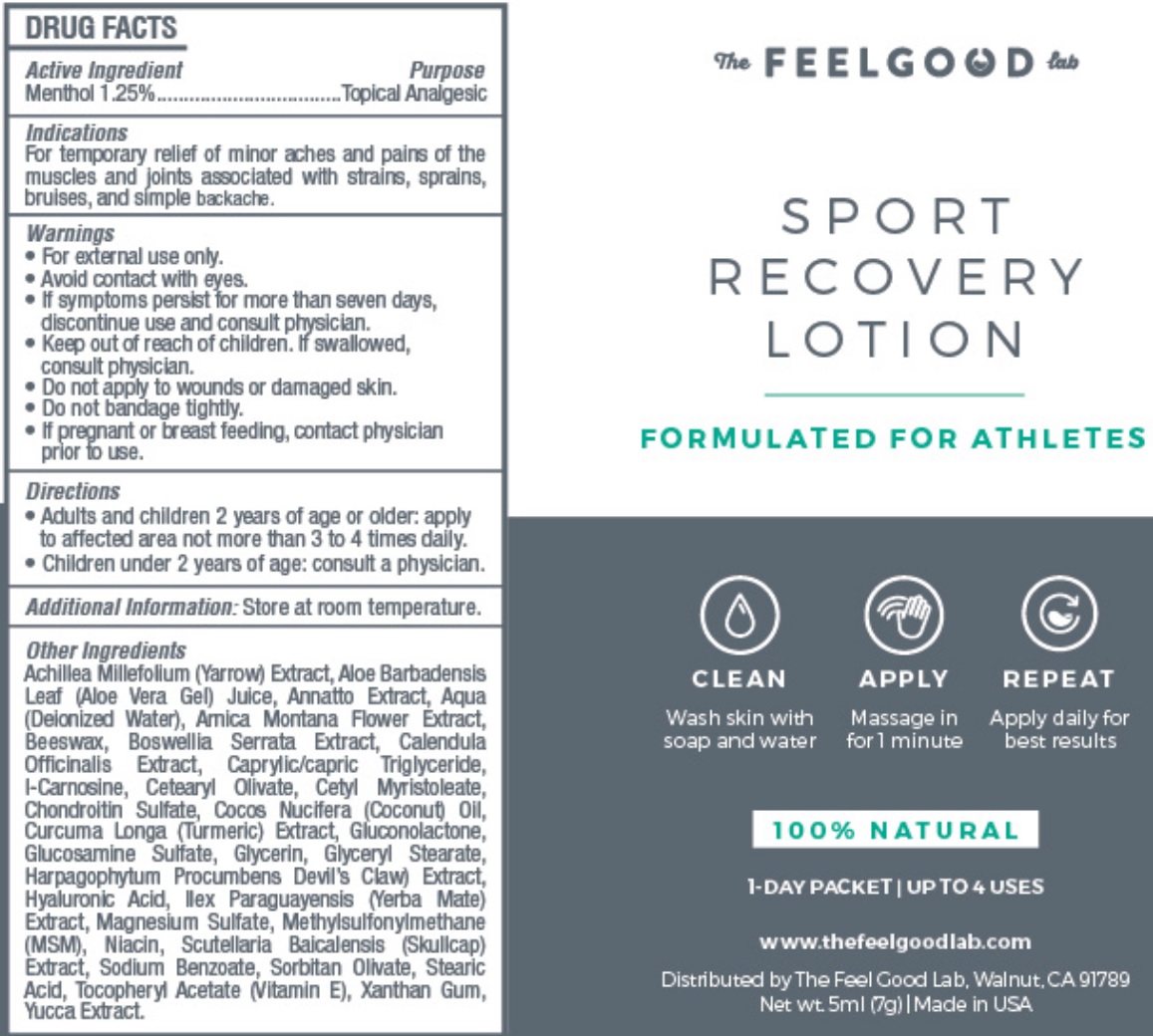 DRUG LABEL: FEEL GOOD LABS SPORT RECOVERY
NDC: 70554-261 | Form: LOTION
Manufacturer: The Feel Good Lab
Category: otc | Type: HUMAN OTC DRUG LABEL
Date: 20231105

ACTIVE INGREDIENTS: MENTHOL 12.5 mg/1 mL
INACTIVE INGREDIENTS: ALOE VERA LEAF; ANNATTO; WATER; ARNICA MONTANA FLOWER; YELLOW WAX; CALENDULA OFFICINALIS FLOWER; MEDIUM-CHAIN TRIGLYCERIDES; CARNOSINE; CETEARYL OLIVATE; CETYL MYRISTOLEATE; COCONUT OIL; TURMERIC; GLUCONOLACTONE; GLUCOSAMINE SULFATE; GLYCERIN; GLYCERYL MONOSTEARATE; HARPAGOPHYTUM PROCUMBENS ROOT; HYALURONIC ACID; ILEX PARAGUARIENSIS LEAF; MAGNESIUM SULFATE, UNSPECIFIED FORM; DIMETHYL SULFONE; NIACIN; SCUTELLARIA BAICALENSIS ROOT; SODIUM BENZOATE; SORBITAN OLIVATE; STEARIC ACID; .ALPHA.-TOCOPHEROL ACETATE, D-; XANTHAN GUM; YUCCA SCHIDIGERA

FEEL GOOD LABS SPORT RECOVERY LOTION

Active Ingredient:

Menthol 1.25%

Purpose

Topical Analgesic

Indications:

For temporary relief of minor aches and pains of the muscles and joints associated with strains, sprains, bruises, and simple backache.

Warnings:

- For external use only.
- Avoid contact with eyes.
- If symptoms persist for more than seven days, discontinue use and consult physician.

Keep out of reach of children.

- If swallowed, consult physician.

Do not apply

- to wounds or damaged skin.
- Do not bandage tightly.

If pregnant or breast feeding,

contact physician prior to use.

Directions

- Adults and children 2 years of age or older: apply to affected area not more than 3 to 4 times daily.
- Children under 2 years of age: consult a physician.

Additional Information:

Store at room temperature.

Other Ingredients:

Achillea Millefolium (Yarrow) Extract, Aloe Barbadensis Leaf (Aloe Vera Gel) Juice, Annatto Extract, Aqua (Deionized Water), Arnica Montana Flower Extract, Beeswax, Boswellia Serrata Extract, Calendula Officinalis Extract, Caprylic/Capric Triglyceride, I-Carnosine, Cetearyl Olivate, Cetyl Myristoleate, Chondroitin Sulfate, Cocos Nucifera (Coconut) Oil, Curcuma Longa (Turmeric) Extract, Gluconolactone, Glucosamine Sulfate, Glycerin, Glyceryl Stearate, Harpagophytum Procumbens (Devil's Claw) Extract, Hyaluronic Acid, Ilex Paraguariensis (Yerba Mate) Extract, Magnesium Sulfate, Methylsulfonylmethane (MSM), Niacin, Scutellaria Baicalensis (Skullcap) Extract, Sodium Benzoate, Sorbitan Olivate, Stearic Acid, Tocopheryl Acetate (Vitamin E), Xanthan Gum, Yucca Extract.